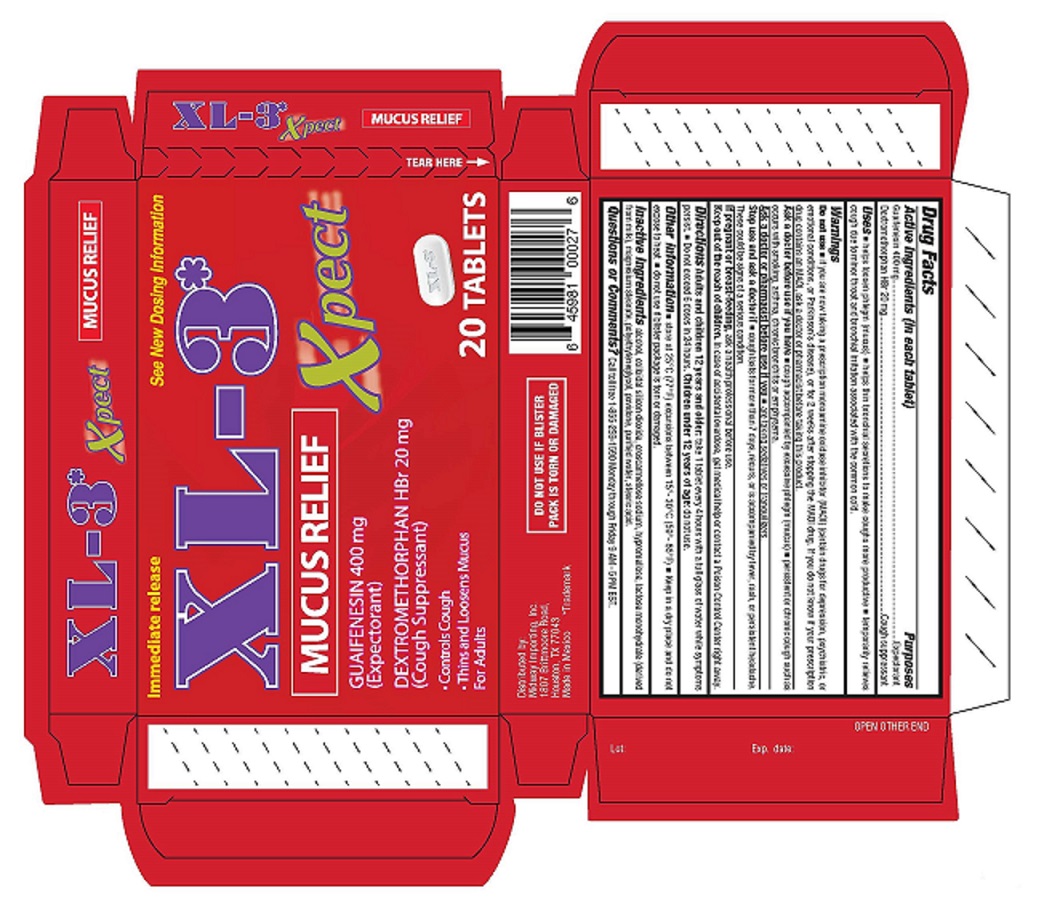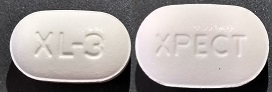 DRUG LABEL: Mucus Relief Xpect
NDC: 76095-012 | Form: TABLET
Manufacturer: Midway Importing Inc.
Category: otc | Type: HUMAN OTC DRUG LABEL
Date: 20241017

ACTIVE INGREDIENTS: GUAIFENESIN 400 mg/1 1; DEXTROMETHORPHAN HYDROBROMIDE 20 mg/1 1
INACTIVE INGREDIENTS: ALCOHOL; POLYETHYLENE GLYCOL, UNSPECIFIED; CROSCARMELLOSE SODIUM; HYPROMELLOSE, UNSPECIFIED; LACTOSE MONOHYDRATE; POVIDONE; SILICON DIOXIDE; STEARIC ACID; MAGNESIUM STEARATE; WATER

XL3 Xpect Mucus Relief

Active ingredients (in each tablet)

Guaifenesin 400mg
Dextromethorphan HBr 20mg

Purposes

Expectorant
Cough suppressant

Uses

■ helps loosen phlegm (mucus) ■ helps thin bronchial secretions to make coughs more productive ■ temporarily relieves cough due to minor sore throat and bronchial irritation associated with the common cold.

Warnings

Do not use

■ if you are now taking a prescription monoamine oxidase inhibitor (MAOI) (certain drugs for depression, psychiatric, or emotional conditions, or Parkinson’s disease), or for 2 weeks after stopping the MAOI drug.If you do not know if your prescription drug contains a MAOI, ask a doctor or pharmacist before taking this product.

Ask a doctor before use if you have

■ cough accompanied by excessive phlegm (mucus) ■ persistent or chronic cough such as occurs with smoking, asthma, chronic bronchitis or emphysema.

Ask a doctor or pharmacist before use if you

■ are taking sedatives or tranquilizers.

Stop use and ask a doctor if

■ cough lasts for more than 7 days, recurs, or is accompanied by fever, rash, or persistent headache.

These could be signs of a serious condition.

Pregnancy/Breastfeeding

If pregnant or breast-feeding, ask a health professional before use.

Keep out of reach of children

Keep out of the reach of children. In case of accidental overdose, get medical help or contact a Poison Control Center right away.

Directions

Adults and children 12 years and older: take 1 tablet every 4 hours with a full glass of water while symptoms persist. ■ Do not exceed 6 doses in 24 hours. Children under 12 years of age: do not use.

Other information

■ store at 25°C (77°F) excursions between 15°-30°C (59°-86°F) ■ Keep in a dry place and do not expose to heat ■ do not use if blister package is torn or damaged.

Inactive Ingredients

alcohol, colloidal silicon dioxide, croscarmellose sodium, hypromellose, lactose monohydrate (derived from milk), magnesium stearate, polyethylene glycol, povidone, purified water, stearic acid

Questions or Comments?

Call toll free 1-855-259-1590 Monday through Friday 9 AM - 5 PM EST.